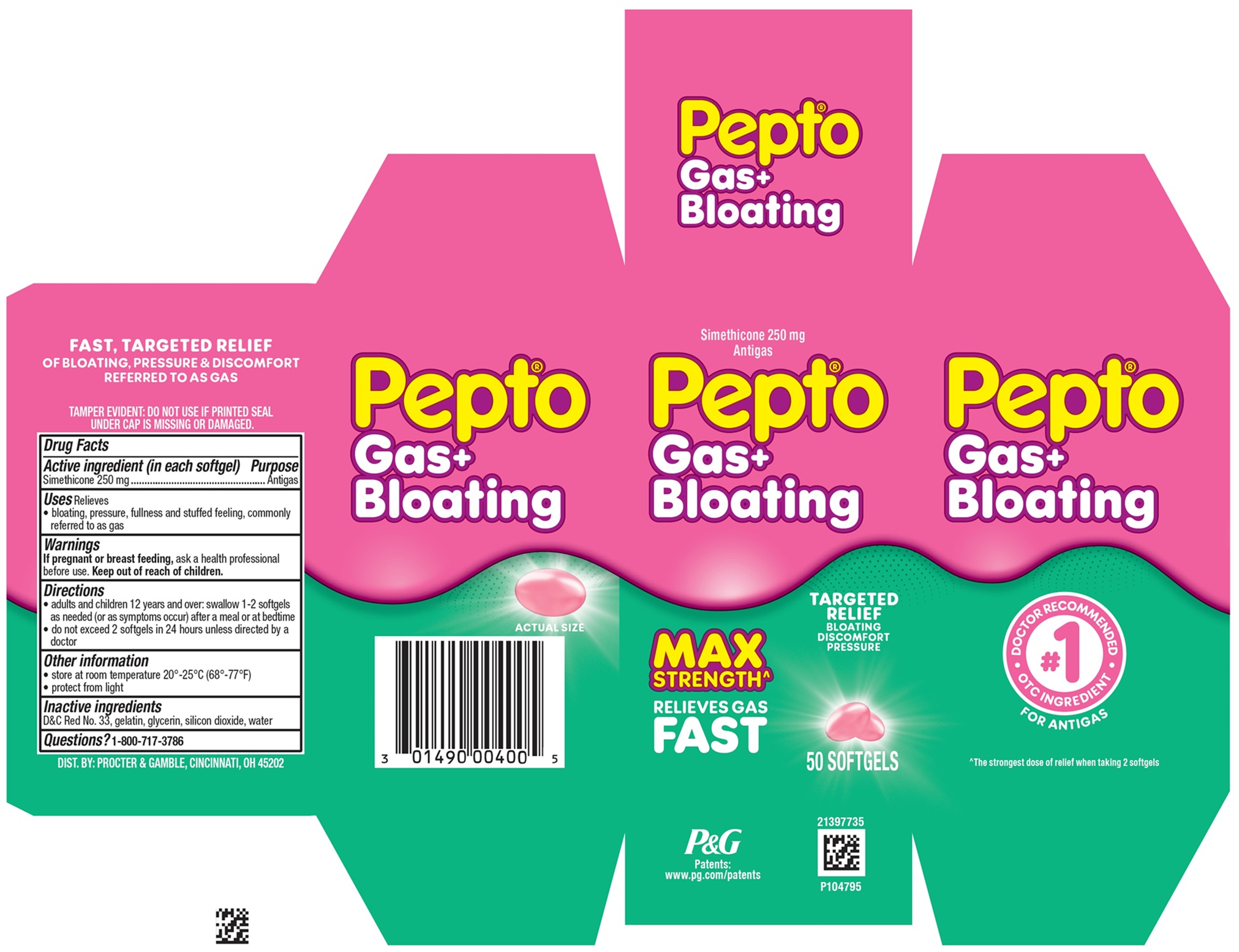 DRUG LABEL: Pepto
NDC: 84126-368 | Form: CAPSULE, LIQUID FILLED
Manufacturer: The Procter & Gamble Manufacturing Company
Category: otc | Type: HUMAN OTC DRUG LABEL
Date: 20251001

ACTIVE INGREDIENTS: DIMETHICONE 250 mg/1 1
INACTIVE INGREDIENTS: GELATIN; WATER; D&C RED NO. 33; SILICON DIOXIDE; GLYCERIN

Pepto® Gas + Bloating

Drug Facts

Active ingredient (in each softgel)

Simethicone 250 mg

Purpose

Antigas

Uses

relieves

- bloating, pressure, fullness and stuffed feeling, commonly referred to as gas

Warnings

If pregnant or breast feeding,

ask a health professional before use.

Keep out of reach of children.

Directions

- adults and children 12 years and over: swallow 1-2 softgels as needed (or as symptoms occur) after a meal or at bedtime
- do not exceed 2 softgels in 24 hours unless directed by a doctor

Other information

- store at room temperature 20°-25°C (68°-77ºF)
- protect from light

Inactive ingredients

D&C Red No. 33, gelatin, glycerin, silicon dioxide, water

Questions?

1-800-717-3786

TAMPER EVIDENT: DO NOT USE IF PRINTED SEAL UNDER CAP IS MISSING OR DAMAGED.

MADE IN CANADA

DIST. BY PROCTER & GAMBLE,

CINCINNATI OH 45202

PRINCIPAL DISPLAY PANEL - 50 Softgels Carton

Simethicone 250 mg Antigas

Pepto Gas + Bloating

TARGETED RELIEF

BLOATING

DISCOMFORT

PRESSURE

MAX STRENGTH

RELIEVES GAS FAST

50 SOFTGELS